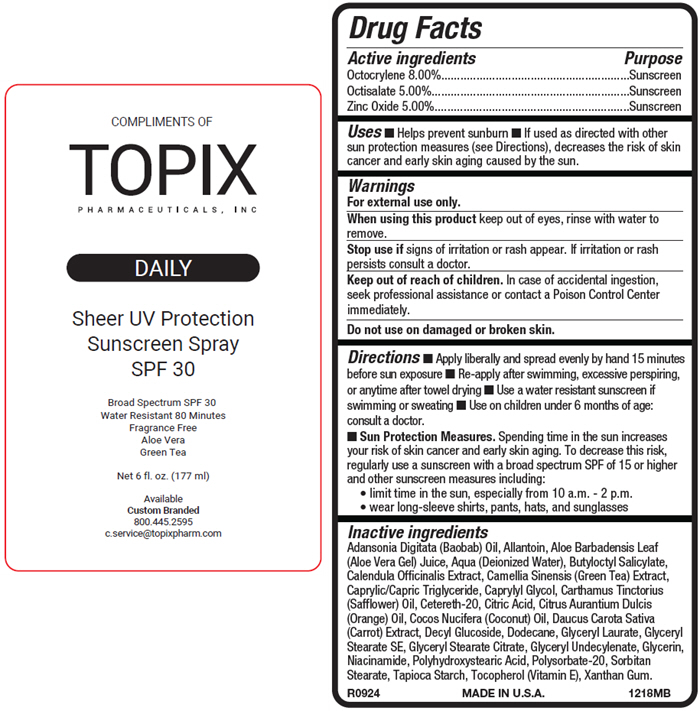 DRUG LABEL: Hybrid SPF
NDC: 51326-128 | Form: SPRAY
Manufacturer: Topiderm, Inc.
Category: otc | Type: HUMAN OTC DRUG LABEL
Date: 20260105

ACTIVE INGREDIENTS: OCTOCRYLENE 80 mg/1 mL; OCTISALATE 50 mg/1 mL; ZINC OXIDE 50 mg/1 mL
INACTIVE INGREDIENTS: ALLANTOIN; ALOE VERA LEAF; ADANSONIA DIGITATA SEED OIL; BUTYLOCTYL SALICYLATE; CALENDULA OFFICINALIS SEED OIL; GREEN TEA LEAF; MEDIUM-CHAIN TRIGLYCERIDES; CAPRYLYL GLYCOL; SAFFLOWER OIL; POLYOXYL 20 CETOSTEARYL ETHER; CITRIC ACID MONOHYDRATE; CITRUS AURANTIUM FRUIT OIL; COCONUT OIL; CARROT JUICE; DECYL GLUCOSIDE; DODECANE; GLYCERYL LAURATE; GLYCERYL STEARATE CITRATE; GLYCERYL MONOSTEARATE; GLYCERIN; NIACINAMIDE; POLYHYDROXYSTEARIC ACID (2300 MW); POLYSORBATE 20; SORBITAN MONOSTEARATE; STARCH, TAPIOCA; .ALPHA.-TOCOPHEROL; GLYCERYL 1-UNDECYLENATE; XANTHAN GUM

Hybrid SPF
SPF 30

Drug Facts

ACTIVE INGREDIENT

Active ingredients | Purpose
Octocrylene 8.00% | Sunscreen
Octisalate 5.00% | Sunscreen
Zinc Oxide 5.00% | Sunscreen

Uses

- Helps prevent sunburn
- If used as directed with other sun protection measures (see Directions), decreases the risk of skin cancer and early skin aging caused by the sun.

Warnings

For external use only.

When using this product keep out of eyes, rinse with water to remove.

Stop use if signs of irritation or rash appear. If irritation or rash persists consult a doctor.

Keep out of reach of children. In case of accidental ingestion, seek professional assistance or contact a Poison Control Center immediately.

Do not use on damaged or broken skin.

Directions

- Apply liberally and spread evenly by hand 15 minutes before sun exposure
- Re-apply after swimming, excessive perspiring, or anytime after towel drying
- Use a water resistant sunscreen if swimming or sweating
- Use on children under 6 months of age: consult a doctor.
- Sun Protection Measures. Spending time in the sun increases your risk of skin cancer and early skin aging. To decrease this risk, regularly use a sunscreen with a broad spectrum SPF of 15 or higher and other sunscreen measures including:
  - limit time in the sun, especially from 10 a.m. - 2 p.m.
  - wear long-sleeve shirts, pants, hats, and sunglasses

Inactive ingredients

Adansonia Digitata (Baobab) Oil, Allantoin, Aloe Barbadensis Leaf (Aloe Vera Gel) Juice, Aqua (Deionized Water), Butyloctyl Salicylate, Calendula Ofﬁcinalis Extract, Camellia Sinensis (Green Tea) Extract, Caprylic/Capric Triglyceride, Caprylyl Glycol, Carthamus Tinctorius (Safﬂower) Oil, Cetereth-20, Citric Acid, Citrus Aurantium Dulcis (Orange) Oil, Cocos Nucifera (Coconut) Oil, Daucus Carota Sativa (Carrot) Extract, Decyl Glucoside, Dodecane, Glyceryl Laurate, Glyceryl Stearate SE, Glyceryl Stearate Citrate, Glyceryl Undecylenate, Glycerin, Niacinamide, Polyhydroxystearic Acid, Polysorbate-20, Sorbitan Stearate, Tapioca Starch, Tocopherol (Vitamin E), Xanthan Gum.

PRINCIPAL DISPLAY PANEL - 177 ml Can Label

COMPLIMENTS OF
TOPIX
PHARMACEUTICALS, INC

DAILY

Sheer UV Protection
Sunscreen Spray
SPF 30

Broad Spectrum SPF 30
Water Resistant 80 Minutes
Fragrance Free
Aloe Vera
Green Tea

Net 6 fl. oz. (177 ml)

Available
Custom Branded
800.445.2595
c.service@topixpharm.com